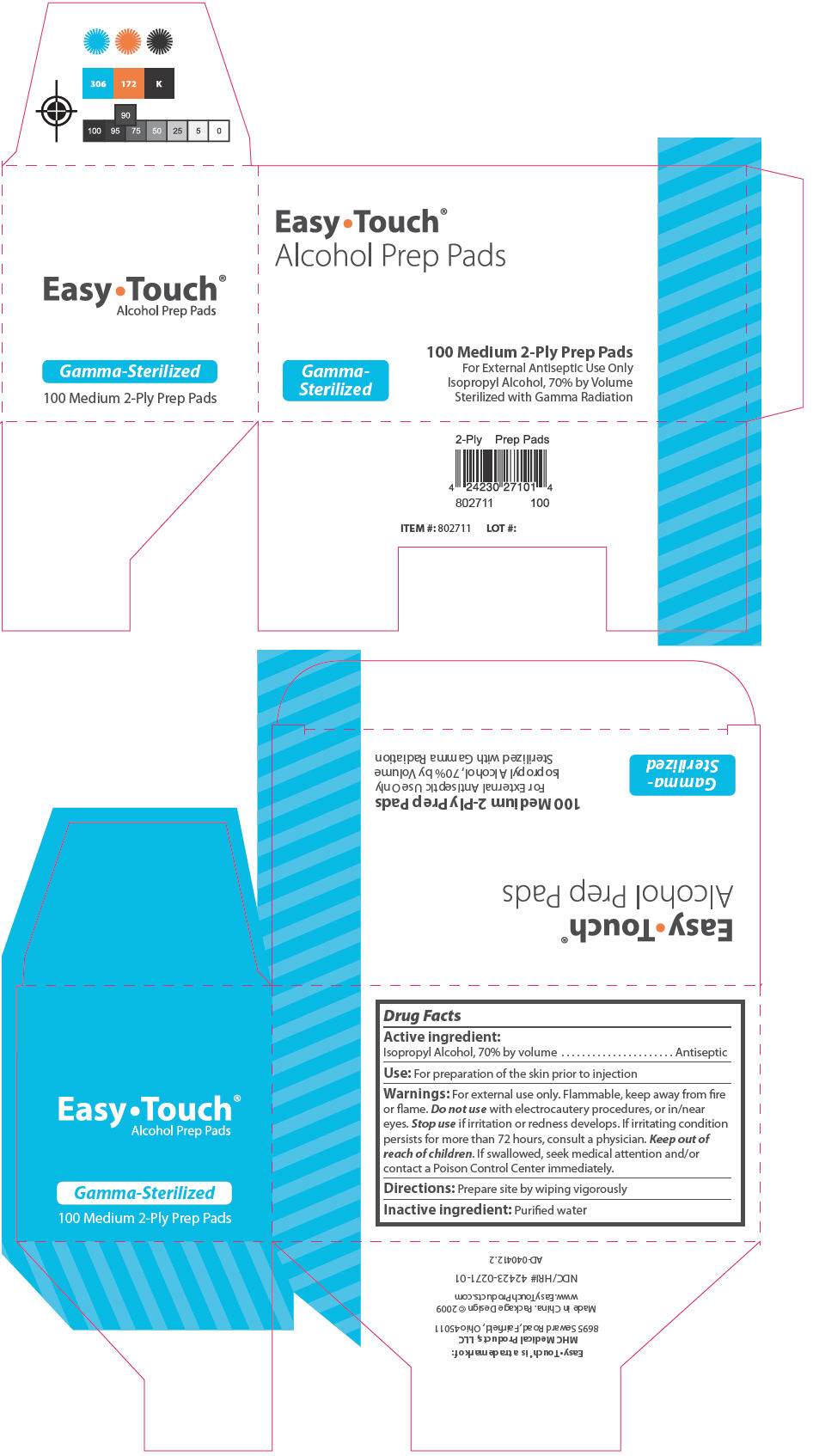 DRUG LABEL: EasyTouch Alcohol Prep Pads 
NDC: 42423-271 | Form: SWAB
Manufacturer: MHC Medical Products, LLC
Category: otc | Type: HUMAN OTC DRUG LABEL
Date: 20251024

ACTIVE INGREDIENTS: Isopropyl Alcohol 70 mL/100 mL
INACTIVE INGREDIENTS: Water

Easy•Touch® Alcohol Prep Pads, Sterile

Drug Facts

Active ingredient

Isopropyl Alcohol, 70% by volume

PURPOSE

Antiseptic

Use

For preparation of the skin prior to injection

Warnings

For external use only. Flammable, keep away from fire or flame.

Do not use with electrocautery procedures, or in/near eyes.

Stop use if irritation or redness develops.

ASK DOCTOR

If irritating condition persists for more than 72 hours, consult a physician.

Keep out of reach of children. If swallowed, seek medical attention and/or contact a Poison Control Center immediately.

Directions

Prepare site by wiping vigorously

Inactive ingredient

Purified water

PRINCIPAL DISPLAY PANEL - 100 Medium 2-Ply Prep Pads Carton

Easy∙Touch®
Alcohol Prep Pads

Gamma-
Sterilized

100 Medium 2-Ply Prep Pads
For External Antiseptic Use Only
Isopropyl Alcohol, 70% by Volume
Sterilized with Gamma Radiation